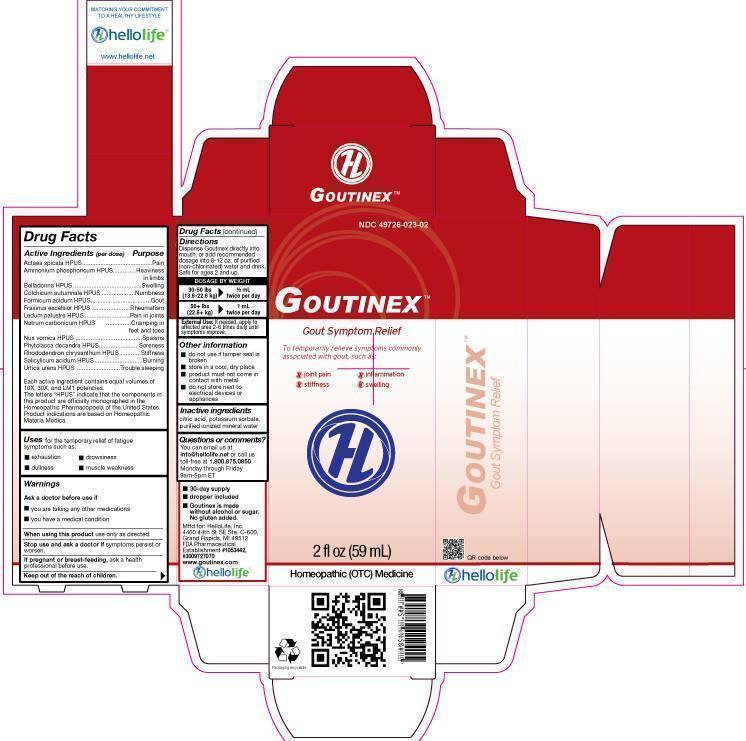 DRUG LABEL: Goutinex
NDC: 49726-023 | Form: LIQUID
Manufacturer: Hello Life, Inc.
Category: homeopathic | Type: HUMAN OTC DRUG LABEL
Date: 20181226

ACTIVE INGREDIENTS: ACTAEA SPICATA ROOT 10 [hp_X]/59 mL; AMMONIUM PHOSPHATE, DIBASIC 10 [hp_X]/59 mL; ATROPA BELLADONNA 10 [hp_X]/59 mL; COLCHICUM AUTUMNALE BULB 10 [hp_X]/59 mL; FORMIC ACID 10 [hp_X]/59 mL; SODIUM CARBONATE 10 [hp_X]/59 mL; STRYCHNOS NUX-VOMICA SEED 10 [hp_X]/59 mL; PHYTOLACCA AMERICANA ROOT 10 [hp_X]/59 mL; RHODODENDRON AUREUM LEAF 10 [hp_X]/59 mL; SALICYLIC ACID 10 [hp_X]/59 mL; URTICA URENS 10 [hp_X]/59 mL; LEDUM PALUSTRE TWIG 10 [hp_X]/59 mL; FRAXINUS EXCELSIOR LEAF 10 [hp_X]/59 mL
INACTIVE INGREDIENTS: WATER; POTASSIUM SORBATE; CITRIC ACID MONOHYDRATE

Drug Facts

Active Ingredients (per dose)

Actaea spicata HPUS
Ammonium phoshoricum HPUS
Belladonna HPUS
Colchicum autumnale HPUS
Formicum acidum HPUS
Fraxinus excelsior HPUS
Ledum palustre HPUS
Natrum carbonicum HPUS
Nux vomica HPUS
Phytolacca decandra HPUS
Rhododendron chrysanthum HPUS
Salicylicum acidum HPUS
Urtica urens HPUS
Each active ingredient contains equal volumes of 10X, 30X, and LM1 potencies.
The letters “HPUS” indicate that the components in this product are officially monographed in the Homeopathic Pharmacopoeia of the United States.
Product indications are based on Homeopathic Materia Medica.

Active Ingredients (per dose)

Actaea spicata HPUS

Ammonium phoshoricum HPUS

Belladonna HPUS

Colchicum autumnale HPUS

Formicum acidum HPUS

Fraxinus excelsior HPUS

Ledum palustre HPUS

Natrum carbonicum HPUS

Nux vomica HPUS

Phytolacca decandra HPUS

Rhododendron chrysanthum HPUS

Salicylicum acidum HPUS

Urtica urens HPUS

Each active ingredient contains equal volumes of 10X, 30X, and LM1 potencies. The letters “HPUS” indicate that the components in this product are officially monographed in the Homeopathic Pharmacopoeia of the United States.

Product indications are based on Homeopathic Materia Medica.

Purpose

Actaea spicata HPUS..……………………….Pain
Ammonium phoshoricum HPUS…......……..Heaviness of limbs
Belladonna HPUS……………………….…...Swelling
Colchicum autumnale HPUS………….........Numbness
Formicum acidum HPUS…………………....Gout
Fraxinus excelsior HPUS.…………………..Rheumatism
Ledum palustre HPUS.………………………Pain in joints
Natrum carbonicum HPUS………..………...Cramping in feet and toes
Nux vomica HPUS……………………………Spasms
Phytolacca decandra HPUS………………...Soreness
Rhododendron chrysanthum HPUS……......Stiffness
Salicylicum acidum HPUS……………………Burning
Urtica urens HPUS…………………………….Trouble sleeping

Uses

to temporarily relieve symptoms commonly associated with gout, such as

- exhaustion
- dullness
- drowsiness
- muscle weakness

Warnings

Ask a doctor before use if

- you are taking any other medications
- you have a medical condition

When using this product, use only as directed.

Stop use and ask a doctor if symptoms persist or worsen.

PREGNANCY OR BREAST FEEDING

If pregnant or breast-feeding, take only on advice of physician.

Keep out of the reach of children.

Directions

Dispense Goutinex directly into mouth, or add recommended dosage into 8-12 oz. of purified (non-chlorinated) water and drink. Safe for ages 2 and up.

DOSAGE BY WEIGHT

30-50 lbs 1/2 mL
(13.6-22.6 kg) twice per day
50+ lbs 1 mL
(22.6+ kg) twice per day

Other information

- do not use if tamper seal is broken

- store in a cool, dry place

- product must not come in contact with metal

- do not store next to electrical devices or appliances

Inactive Ingredients

citric acid, potassium sorbate, purified ionized mineral water.

Questions or comments?

You can email us at info@hellolife.net or call us toll-free at 1.800.875.0850 Monday through Friday, 9am-5pm ET.

DESCRIPTION

- 30-day supply
- dropper included
- Goutinex is made without alcohol or sugar; no gluten added.

Mftd for: HelloLife, Inc.
4460 44th St. SE, Ste. C-600
Grand Rapids, MI 49512
FDA Pharmaceutical Establishment
#1053442, #3009727070
www.goutinex.com

Principal Display Panel

NDC 49726-023-02

GOUTINEX™

Gout Symptom Relief

To temporarily relieve symptoms commonly associated with gout, such as:

- joint pain
- stiffness
- inflammation
- swelling

Homeopathic (OTC) Medicine
2 fl oz (59 mL)